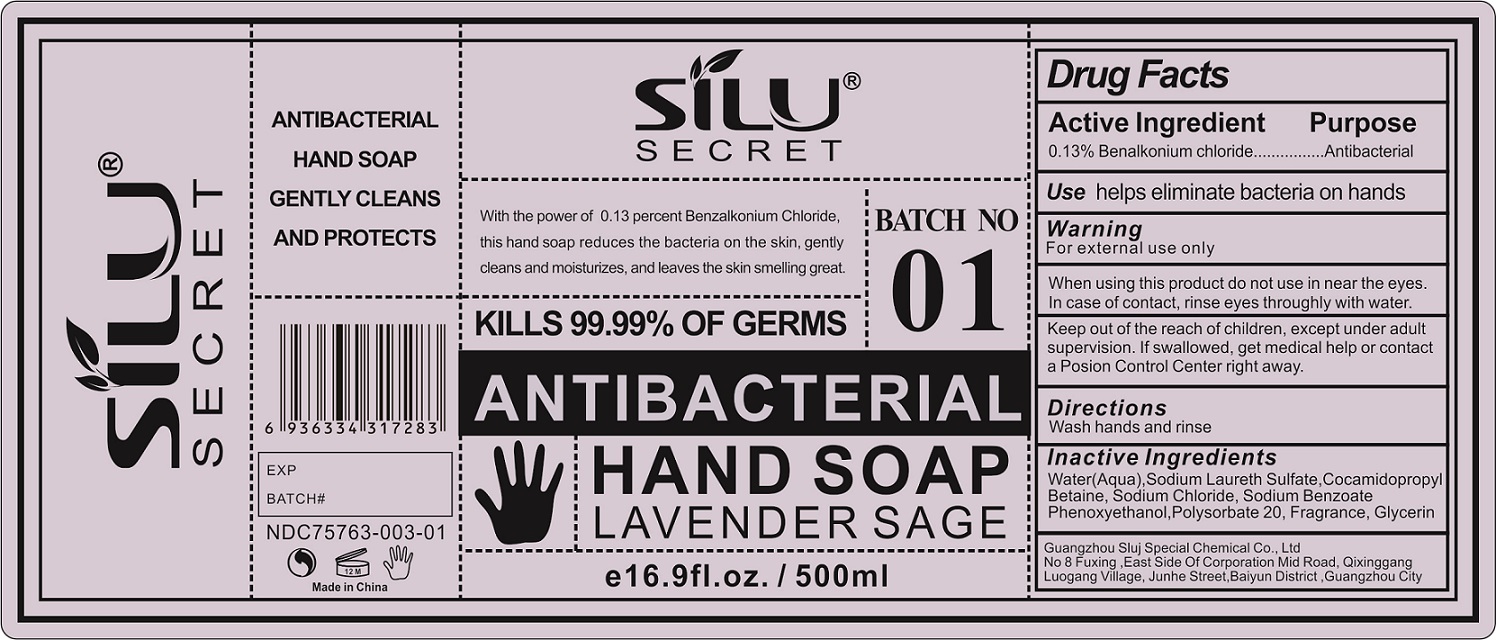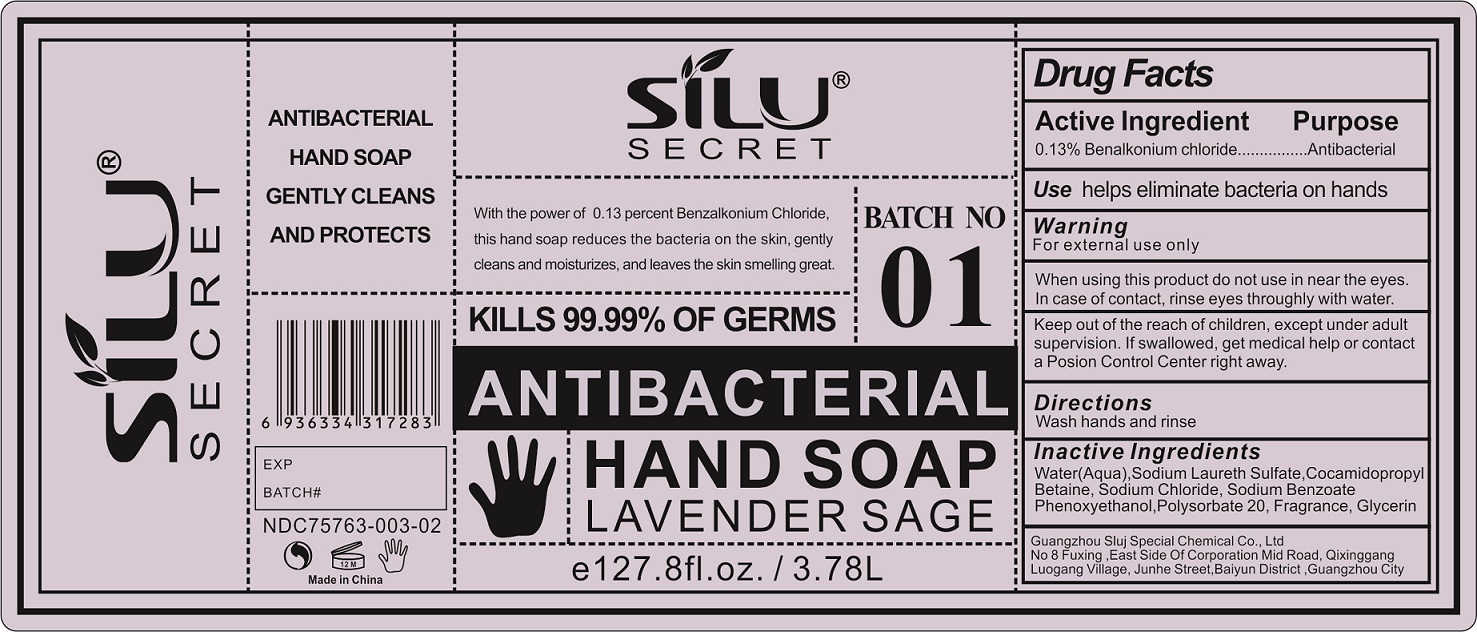 DRUG LABEL: Antibacterial Hand Lavender Sage
NDC: 78784-003 | Form: LIQUID
Manufacturer: GUANGZHOU SLUJ SPECIAL CHEMICAL CO., LTD
Category: otc | Type: HUMAN OTC DRUG LABEL
Date: 20230223

ACTIVE INGREDIENTS: BENZALKONIUM CHLORIDE 1.3 mg/1 mL
INACTIVE INGREDIENTS: WATER; SODIUM LAURETH SULFATE; COCAMIDOPROPYL BETAINE; SODIUM CHLORIDE; SODIUM BENZOATE; PHENOXYETHANOL; POLYSORBATE 20; GLYCERIN

Antibacterial Hand Soap Lavender Sage

Active Ingredient

0.13% Benalkonium chloride

Purpose

Antibacterial

Use

helps eliminate bacteria on hands

Warnings

For external use only

When using this product

do not use in near the eyes. In case of contact, rinse eyes throughly with water.

Keep out of the reach of children,

except under adult supervision. If swallowed, get medical help or contact a Poison Control Center right away.

Directions

Wash hands and rinse

Inactive Ingredients

Water(Aqua),Sodium Laureth Sulfate,Cocamidopropyl Betaine, Sodium Chloride, Sodium Benzoate Phenoxyethanol,Polysorbate 20, Fragrance, Glycerin